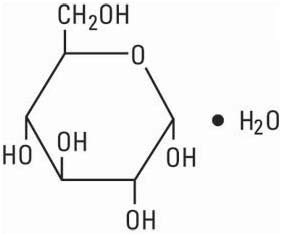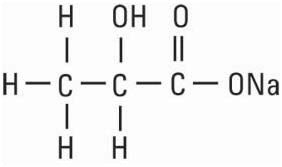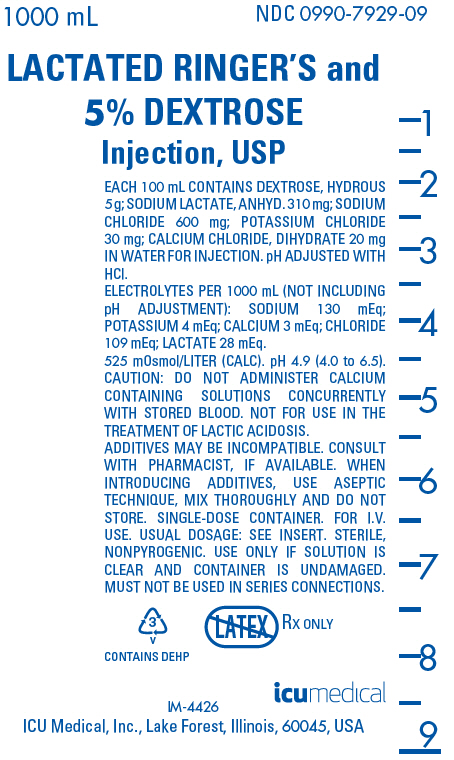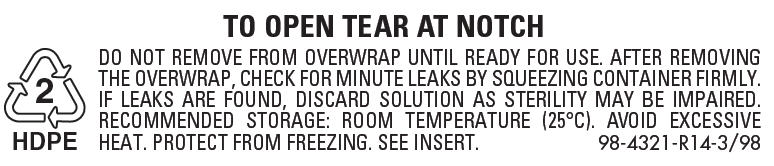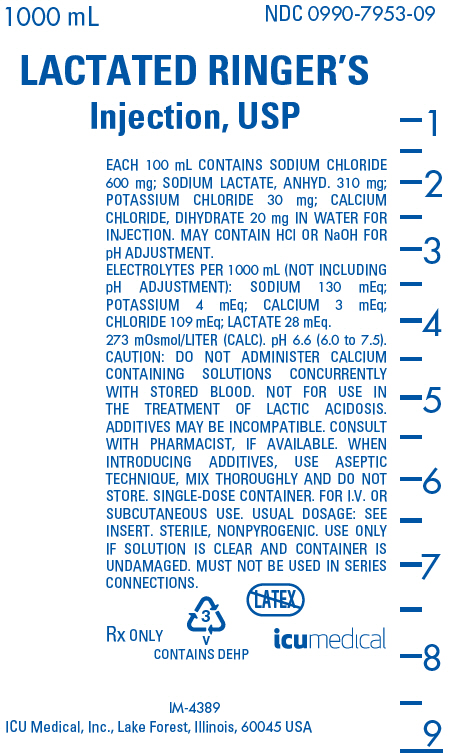 DRUG LABEL: Lactated Ringers and Dextrose
NDC: 0990-7929 | Form: INJECTION, SOLUTION
Manufacturer: ICU Medical Inc.
Category: prescription | Type: HUMAN PRESCRIPTION DRUG LABEL
Date: 20251102

ACTIVE INGREDIENTS: SODIUM CHLORIDE 600 mg/100 mL; SODIUM LACTATE 310 mg/100 mL; POTASSIUM CHLORIDE 30 mg/100 mL; CALCIUM CHLORIDE 20 mg/100 mL; DEXTROSE MONOHYDRATE 5 g/100 mL
INACTIVE INGREDIENTS: HYDROCHLORIC ACID

Lactated Ringer's Injection, USP
Lactated Ringer's and 5% Dextrose Injection, USP

Flexible Plastic Container

Rx only

DESCRIPTION

These products are sterile, nonpyrogenic solutions each containing isotonic concentrations of electrolytes (with or without dextrose) in water for injection. The solutions containing dextrose and electrolytes are hypertonic; those containing only electrolytes are isotonic. They are administered by intravenous infusion for parenteral replacement of extracellular losses of fluid and electrolytes, with or without minimal carbohydrate calories.

Each 100 mL of Lactated Ringer's Injection, USP contains sodium chloride 600 mg, sodium lactate, anhydrous 310 mg, potassium chloride 30 mg and calcium chloride, dihydrate 20 mg. May contain hydrochloric acid and/or sodium hydroxide for pH adjustment. A liter provides 9 calories (from lactate), sodium (Na^+), 130 mEq, potassium (K^+) 4 mEq, calcium (Ca^++) 3 mEq, chloride (Cl^−) 109 mEq and lactate [CH3CH(OH) COO^−] 28 mEq. The electrolyte content is isotonic (273 mOsmol/liter, calc.) in relation to the extracellular fluid (approx. 280 mOsmol/liter). The pH of the solution is 6.6 (6.0 − 7.5).

Each 100 mL of Lactated Ringer's and 5% Dextrose Injection, USP contains dextrose, hydrous 5 g plus the same ingredients and mEq values as Lactated Ringer's Injection, USP (contains only hydrochloric acid for pH adjustment). A liter provides 179 calories (from dextrose and lactate) and has a hypertonic osmolar concentration of 525 mOsmol (calc.). The pH is 4.9 (4.0 − 6.5).

The solutions contain no bacteriostat, antimicrobial agent or added buffer (except for pH adjustment) and each is intended only for use as a single-dose injection. When smaller doses are required the unused portion should be discarded.

The solutions are parenteral fluid, nutrient and/or electrolyte replenishers.

Dextrose, USP is chemically designated D-glucose, monohydrate (C6H12O6 • H2O), a hexose sugar freely soluble in water. It has the following structural formula:

Calcium Chloride, USP is chemically designated calcium chloride, dihydrate (CaCl2 • 2 H2O), white fragments or granules freely soluble in water.

Potassium Chloride, USP is chemically designated KCl, a white granular powder freely soluble in water.

Sodium Chloride, USP is chemically designated NaCl, a white crystalline powder freely soluble in water.

Sodium Lactate, USP is chemically designated monosodium lactate [CH3CH(OH)COONa], a 60% aqueous solution miscible in water.

It has the following structural formula:

Water for Injection, USP is chemically designated H2O.

The flexible plastic container is fabricated from a specially formulated polyvinylchloride. Water can permeate from inside the container into the overwrap but not in amounts sufficient to affect the solution significantly. Solutions inside the plastic container also can leach out certain of their chemical components in very small amounts before the expiration period is attained. However, the safety of the plastic has been confirmed by tests in animals according to USP biological standards for plastic containers.

CLINICAL PHARMACOLOGY

When administered intravenously, these solutions provide sources of water and electrolytes with or without minimal carbohydrate calories. Their electrolyte content resembles that of the principal ionic constituents of normal plasma and the solutions therefore are suitable for parenteral replacement of extracellular losses of fluid and electrolytes, with or without carbohydrate calories.

Solutions containing carbohydrate in the form of dextrose restore blood glucose levels and provide calories.

Carbohydrate in the form of dextrose may aid in minimizing liver glycogen depletion and exerts a protein-sparing action. Dextrose injected parenterally undergoes oxidation to carbon dioxide and water.

Calcium chloride in water dissociates to provide calcium (Ca^++) and chloride (Cl^−) ions. They are normal constituents of the body fluids and are dependent on various physiologic mechanisms for maintenance of balance between intake and output. Approximately 80% of body calcium is excreted in the feces as insoluble salts; urinary excretion accounts for the remaining 20%.

Potassium chloride in water dissociates to provide potassium (K^+) and chloride (Cl^−) ions. Potassium is found in low concentration in plasma and extracellular fluids (3.5 to 5.0 mEq/liter in a healthy adult). It is the chief cation of body cells (160 mEq/liter of intracellular water). Potassium plays an important role in electrolyte balance. Normally about 80 to 90% of the potassium intake is excreted in the urine; the remainder in the stools and to a small extent, in the perspiration. The kidney does not conserve potassium well so that during fasting or in patients on a potassium-free diet, potassium loss from the body continues resulting in potassium depletion.

Sodium chloride in water dissociates to provide sodium (Na^+) and chloride (Cl^−) ions. Sodium (Na^+) is the principal cation of the extracellular fluid and plays a large part in the therapy of fluid and electrolyte disturbances. Chloride (Cl^−) has an integral role in buffering action when oxygen and carbon dioxide exchange occurs in the red blood cells. The distribution and excretion of sodium (Na+) and chloride (Cl^−) are largely under the control of the kidney which maintains a balance between intake and output.

Sodium lactate provides sodium (Na^+) and lactate (C3H503^−) ions. The lactate anion is in equilibrium with pyruvate and has an alkalizing effect resulting from simultaneous removal by the liver of lactate and hydrogen ions. In the liver, lactate is metabolized to glycogen which is ultimately converted to carbon dioxide and water by oxidative metabolism. The sodium (Na^+) ion combines with bicarbonate ion produced from carbon dioxide of the body and thus retains bicarbonate to combat metabolic acidosis (bicarbonate deficiency). The normal plasma level of lactate ranges from 0.9 to 1.9 mEq/liter.

Water is an essential constituent of all body tissues and accounts for approximately 70% of total body weight. Average normal adult daily requirement ranges from two to three liters (1.0 to 1.5 liters each for insensible water loss by perspiration and urine production).

Water balance is maintained by various regulatory mechanisms. Water distribution depends primarily on the concentration of electrolytes in the body compartments and sodium (Na^+) plays a major role in maintaining physiologic equilibrium.

INDICATIONS AND USAGE

These solutions are indicated for parenteral replacement of extracellular losses of fluid and electrolytes, with or without minimal carbohydrate calories, as required by the clinical condition of the patient.

CONTRAINDICATIONS

Solutions containing lactate are NOT FOR USE IN THE TREATMENT OF LACTIC ACIDOSIS.

WARNINGS

Solutions containing calcium ions should not be administered simultaneously through the same administration set as blood because of the likelihood of coagulation.

Solutions which contain potassium should be used with great care, if at all, in patients with hyperkalemia, severe renal failure and in conditions in which potassium retention is present.

Solutions containing sodium ions should be used with great care, if at all, in patients with congestive heart failure, severe renal insufficiency and in clinical states in which there exists edema with sodium retention.

In patients with diminished renal function, administration of solutions containing sodium or potassium ions may result in sodium or potassium retention.

Solutions containing lactate ions should be used with great care in patients with metabolic or respiratory alkalosis. The administration of lactate ions should be done with great care where there is an increased level or an impaired utilization of lactate ions, as in severe hepatic insufficiency.

The intravenous administration of these solutions can cause fluid and/or solute overloading resulting in dilution of serum electrolyte concentrations, overhydration, congested states or pulmonary edema. The risk of dilutional states is inversely proportional to the electrolyte concentrations of administered parenteral solutions.

The risk of solute overload causing congested states with peripheral and pulmonary edema is directly proportional to the electrolyte concentrations of such solutions.

PRECAUTIONS

Clinical evaluation and periodic laboratory determinations are necessary to monitor changes in fluid balance, electrolyte concentrations and acid-base balance during prolonged parenteral therapy or whenever the condition of the patient warrants such evaluation.

Solutions containing dextrose should be used with caution in patients with known subclinical or overt diabetes mellitus.

Caution must be exercised in the administration of parenteral fluids, especially those containing sodium ions, to patients receiving corticosteroids or corticotropin.

Potassium containing solutions should be used with caution in the presence of cardiac disease, particularly in digitalized patients or in the presence of renal disease.

Solutions containing lactate ions should be used with caution as excess administration may result in metabolic alkalosis.

Do not administer unless solution is clear and container is undamaged. Discard unused portion.

PREGNANCY

Pregnancy Category C. Animal reproduction studies have not been conducted with Ringer's Injection, USP, Ringer's and Dextrose Injection, USP, Lactated Ringer's Injection, USP or Lactated Ringer's and Dextrose Injection, USP. It is also not known whether these injections can cause fetal harm when administered to a pregnant woman or can affect reproduction capacity. These injections should be given to a pregnant woman only if clearly needed.

PEDIATRIC USE

Pediatric Use: The safety and effectiveness in the pediatric population are based on the similarity of the clinical conditions of the pediatric and adult populations. In neonates or very small infants the volume of fluid may affect fluid and electrolyte balance.

Frequent monitoring of serum glucose concentrations is required when dextrose is prescribed to pediatric patients, particularly neonates and low birth weight infants.

In very low birth weight infants, excessive or rapid administration of dextrose injection may result in increased serum osmolarity and possible intracerebral hemorrhage.

ADVERSE REACTIONS

Reactions which may occur because of the solution or the technique of administration include febrile response, infection at the site of injection, venous thrombosis or phlebitis extending from the site of injection, extravasation and hypervolemia.

If an adverse reaction does occur, discontinue the infusion, evaluate the patient, institute appropriate therapeutic countermeasures and save the remainder of the fluid for examination if deemed necessary.

OVERDOSAGE

In the event of overhydration or solute overload, re-evaluate the patient and institute appropriate corrective measures. See WARNINGS, PRECAUTIONS, and ADVERSE REACTIONS.

DOSAGE AND ADMINISTRATION

The dose is dependent upon the age, weight and clinical condition of the patient.

As reported in the literature, the dosage and constant infusion rate of intravenous dextrose must be selected with caution in pediatric patients, particularly neonates and low birth weight infants, because of the increased risk of hyperglycemia/hypoglycemia.

Drug Interactions

Additives may be incompatible. Consult with pharmacist, if available. When introducing additives, use aseptic technique, mix thoroughly and do not store.

The presence of calcium limits their compatibility with certain drugs that form precipitates of calcium salts, and also prohibits their simultaneous infusion through the same administration set as blood because of the likelihood of coagulation.

Parenteral drug products should be inspected visually for particulate matter and discoloration prior to administration, whenever solution and container permit. See PRECAUTIONS.

INSTRUCTIONS FOR USE

To Open:

Tear outer wrap at notch and remove solution container. If supplemental medication is desired, follow directions below before preparing for administration. Some opacity of the plastic due to moisture absorption during the sterilization process may be observed. This is normal and does not affect the solution quality or safety. The opacity will diminish gradually.

To Add Medication

1. Prepare additive port.
2. Using aseptic technique and an additive delivery needle of appropriate length, puncture resealable additive port at target area, inner diaphragm and inject. Withdraw needle after injecting medication.
3. The additive port may be protected by covering with an additive cap.
4. Mix container contents thoroughly.

Preparation for Administration

(Use aseptic technique)

1. Close flow control clamp of administration set.
2. Remove cover from outlet port at bottom of container.
3. Insert piercing pin of administration set into port with a twisting motion until the set is firmly seated. NOTE: See full directions on administration set carton.
4. Suspend container from hanger.
5. Squeeze and release drip chamber to establish proper fluid level in chamber.
6. Open flow control clamp and clear air from set. Close clamp.
7. Attach set to venipuncture device. If device is not indwelling, prime and make venipuncture.
8. Regulate rate of administration with flow control clamp.

WARNING: DO NOT USE FLEXIBLE CONTAINER IN SERIES CONNECTIONS.

HOW SUPPLIED

These solutions are supplied in single-dose flexible plastic containers as follows:

NDC No. | Product Name | Container Size (mL)
0409-7953-02 [Manufactured by ICU Medical, Inc., Lake Forest, Illinois, 60045, USA] | Lactated Ringer's Inj., USP | 250
0990-7953-02 | Lactated Ringer's Inj., USP | 250
0409-7953-03 [Manufactured for ICU Medical, Inc., Lake Forest, Illinois, 60045, USA] | Lactated Ringer's Inj., USP | 500
0990-7953-03, | Lactated Ringer's Inj., USP | 500
0409-7953-09, | Lactated Ringer's Inj., USP | 1000
0990-7953-09, | Lactated Ringer's Inj., USP | 1000
0409-7929-03 | Lactated Ringer's and 5% Dextrose Inj., USP | 500
0990-7929-03, | Lactated Ringer's and 5% Dextrose Inj., USP | 500
0409-7929-09, | Lactated Ringer's and 5% Dextrose Inj., USP | 1000
0990-7929-09, | Lactated Ringer's and 5% Dextrose Inj., USP | 1000

ICU Medical is transitioning NDC codes from "0409" to a"0990" labeler code. Both NDC codes are expected to be in the market for a period of time.

Store at 20 to 25°C (68 to 77°F). [See USP Controlled Room Temperature.] Protect from freezing.

Revised: April, 2020

IFU0000184

PRINCIPAL DISPLAY PANEL - 1000 mL Bag Label - NDC 0990-7929-09

1000 mL
NDC 0990-7929-09

LACTATED RINGER'S and
5% DEXTROSE
Injection, USP

EACH 100 mL CONTAINS DEXTROSE, HYDROUS
5 g; SODIUM LACTATE, ANHYD. 310 mg; SODIUM
CHLORIDE 600 mg; POTASSIUM CHLORIDE
30 mg; CALCIUM CHLORIDE, DIHYDRATE 20 mg
IN WATER FOR INJECTION. pH ADJUSTED WITH
HCl.
ELECTROLYTES PER 1000 mL (NOT INCLUDING
pH ADJUSTMENT): SODIUM 130 mEq;
POTASSIUM 4 mEq; CALCIUM 3 mEq; CHLORIDE
109 mEq; LACTATE 28 mEq.
525 mOsmol/LITER (CALC). pH 4.9 (4.0 to 6.5).
CAUTION: DO NOT ADMINISTER CALCIUM
CONTAINING SOLUTIONS CONCURRENTLY
WITH STORED BLOOD. NOT FOR USE IN THE
TREATMENT OF LACTIC ACIDOSIS.
ADDITIVES MAY BE INCOMPATIBLE. CONSULT
WITH PHARMACIST, IF AVAILABLE. WHEN
INTRODUCING ADDITIVES, USE ASEPTIC
TECHNIQUE, MIX THOROUGHLY AND DO NOT
STORE. SINGLE-DOSE CONTAINER. FOR I.V.
USE. USUAL DOSAGE: SEE INSERT. STERILE,
NONPYROGENIC. USE ONLY IF SOLUTION IS
CLEAR AND CONTAINER IS UNDAMAGED.
MUST NOT BE USED IN SERIES CONNECTIONS.

3
V
CONTAINS DEHP

RX ONLY

icumedical

IM-4426

ICU Medical, Inc., Lake Forest, Illinois, 60045, USA

PRINCIPAL DISPLAY PANEL - 1000 mL Bag Overwrap - NDC 0409-7929-09

TO OPEN TEAR AT NOTCH

2
HDPE

DO NOT REMOVE FROM OVERWRAP UNTIL READY FOR USE. AFTER REMOVING
THE OVERWRAP, CHECK FOR MINUTE LEAKS BY SQUEEZING CONTAINER FIRMLY.
IF LEAKS ARE FOUND, DISCARD SOLUTION AS STERILITY MAY BE IMPAIRED.
RECOMMENDED STORAGE: ROOM TEMPERATURE (25°C). AVOID EXCESSIVE
HEAT. PROTECT FROM FREEZING. SEE INSERT.
98-4321-R14-3/98

PRINCIPAL DISPLAY PANEL - 1000 mL Bag Label - NDC 0990-7953-09

1000 mL
NDC 0990-7953-09

LACTATED RINGER'S
Injection, USP

EACH 100 mL CONTAINS SODIUM CHLORIDE
600 mg; SODIUM LACTATE, ANHYD. 310 mg;
POTASSIUM CHLORIDE 30 mg; CALCIUM
CHLORIDE, DIHYDRATE 20 mg IN WATER FOR
INJECTION. MAY CONTAIN HCl OR NaOH FOR
pH ADJUSTMENT.
ELECTROLYTES PER 1000 mL (NOT INCLUDING
pH ADJUSTMENT): SODIUM 130 mEq;
POTASSIUM 4 mEq; CALCIUM 3 mEq;
CHLORIDE 109 mEq; LACTATE 28 mEq.
273 mOsmol/LITER (CALC). pH 6.6 (6.0 to 7.5).
CAUTION: DO NOT ADMINISTER CALCIUM
CONTAINING SOLUTIONS CONCURRENTLY
WITH STORED BLOOD. NOT FOR USE IN
THE TREATMENT OF LACTIC ACIDOSIS.
ADDITIVES MAY BE INCOMPATIBLE. CONSULT
WITH PHARMACIST, IF AVAILABLE. WHEN
INTRODUCING ADDITIVES, USE ASEPTIC
TECHNIQUE, MIX THOROUGHLY AND DO NOT
STORE. SINGLE-DOSE CONTAINER. FOR I.V. OR
SUBCUTANEOUS USE. USUAL DOSAGE: SEE
INSERT. STERILE, NONPYROGENIC. USE ONLY
IF SOLUTION IS CLEAR AND CONTAINER IS
UNDAMAGED. MUST NOT BE USED IN SERIES
CONNECTIONS.

RX ONLY

3
V
CONTAINS DEHP

icumedical

IM-4389

ICU Medical, Inc., Lake Forest, Illinois, 60045 USA

PRINCIPAL DISPLAY PANEL - 1000 mL Bag Overwrap - NDC 0409-7953-09

TO OPEN TEAR AT NOTCH

2
HDPE

DO NOT REMOVE FROM OVERWRAP UNTIL READY FOR USE. AFTER REMOVING
THE OVERWRAP, CHECK FOR MINUTE LEAKS BY SQUEEZING CONTAINER FIRMLY.
IF LEAKS ARE FOUND, DISCARD SOLUTION AS STERILITY MAY BE IMPAIRED.
RECOMMENDED STORAGE: ROOM TEMPERATURE (25°C). AVOID EXCESSIVE
HEAT. PROTECT FROM FREEZING. SEE INSERT.
98-4321-R14-3/98